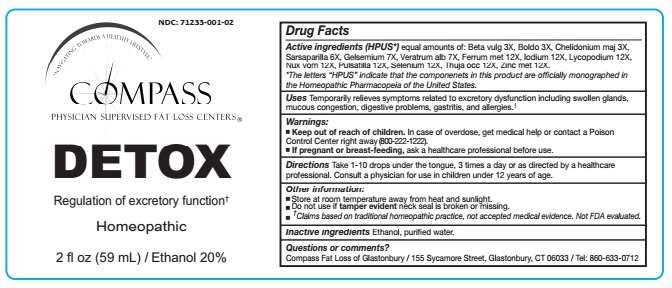 DRUG LABEL: Detox
NDC: 71233-001 | Form: LIQUID
Manufacturer: Compass Fat Loss of Glastonbury LLC
Category: homeopathic | Type: HUMAN OTC DRUG LABEL
Date: 20211229

ACTIVE INGREDIENTS: BETA VULGARIS 3 [hp_X]/59 mL; PEUMUS BOLDUS LEAF 3 [hp_X]/59 mL; CHELIDONIUM MAJUS 3 [hp_X]/59 mL; SMILAX ORNATA ROOT 6 [hp_X]/59 mL; GELSEMIUM SEMPERVIRENS ROOT 7 [hp_X]/59 mL; VERATRUM ALBUM ROOT 7 [hp_X]/59 mL; IRON 12 [hp_X]/59 mL; IODINE 12 [hp_X]/59 mL; LYCOPODIUM CLAVATUM SPORE 12 [hp_X]/59 mL; STRYCHNOS NUX-VOMICA SEED 12 [hp_X]/59 mL; PULSATILLA VULGARIS 12 [hp_X]/59 mL; SELENIUM 12 [hp_X]/59 mL; THUJA OCCIDENTALIS LEAFY TWIG 12 [hp_X]/59 mL; ZINC 12 [hp_X]/59 mL
INACTIVE INGREDIENTS: WATER; ALCOHOL

DETOX

ACTIVE INGREDIENT

Active ingredients (HPUS*) equal amounts of: Beta vulg 3X, Boldo 3X, Chelidonium maj 3X, Sarsaparilla 6X, Gelsemium 7X, Veratrum alb 7X, Ferrum met 12X, Iodium 12X, Lycopodium 12X, Nux vom 12X, Pulsatilla 12X, Selenium 12X, Thuja occ 12X, Zinc met 12X.

*The letters “HPUS” indicate that the componenets in this product are officially monographed in the Homeopathic Pharmacopeia of the United States.

INDICATIONS AND USAGE

Uses Temporarily relieves symptoms related to excretory dysfunction including swollen glands, mucous congestion, digestive problems, gastritis, and allergies.†

Warnings:

- Keep out of reach of children. In case of overdose, get medical help or contact a Poison Control Center right away (800-222-1222).
- If pregnant or breast-feeding, ask a healthcare professional before use.

Keep out of reach of children

DOSAGE AND ADMINISTRATION

Directions Take 1-10 drops under the tongue, 3 times a day or as directed by a healthcare professional. Consult a physician for use in children under 12 years of age.

Other information:

- Store at room temperature away from heat and sunlight.
- Do not use if tamper evident neck seal is broken or missing.
- † Claims based on traditional homeopathic practice, not accepted medical evidence. Not FDA evaluated.

Inactive ingredients Ethanol, purified water.

Questions or comments?
Compass Fat Loss of Glastonbury / 155 Sycamore Street, Glastonbury, CT 06033 / Tel: 860-633-0712

PACKAGE LABEL

NDC: 71233-001-02

COMPASS PHYSICIAN SUPERVISED FAT-LOSS CENTERS®

DETOX

Regulation of excretory function†

Homeopathic

2 fl oz (59mL) / Ethanol 20%

PURPOSE

Regulation of excretory function†